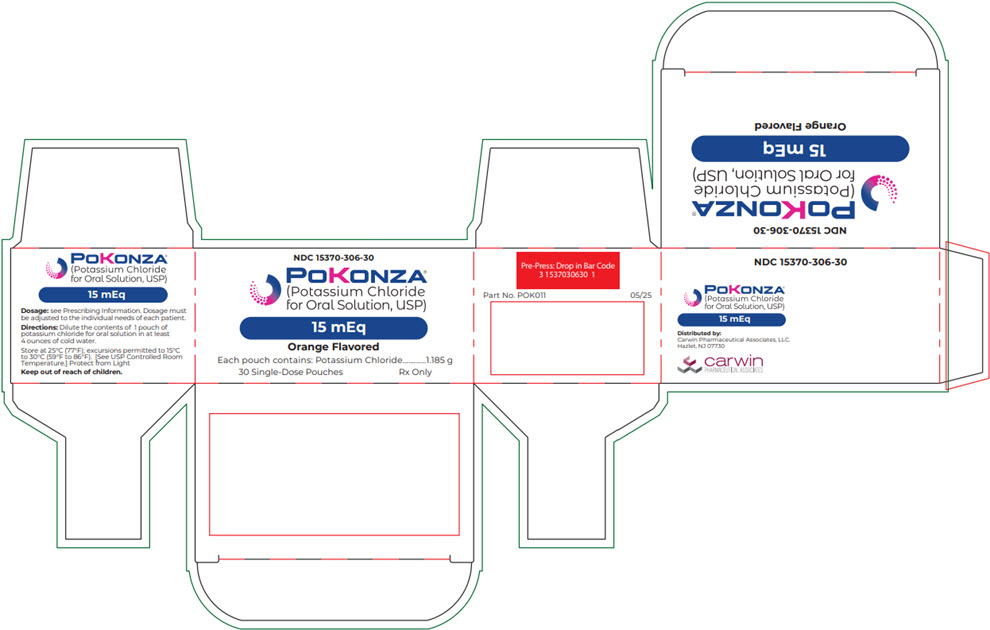 DRUG LABEL: POKONZA
NDC: 15370-306 | Form: POWDER, FOR SOLUTION
Manufacturer: Carwin Pharmaceutical Associates, LLC
Category: prescription | Type: HUMAN PRESCRIPTION DRUG LABEL
Date: 20251218

ACTIVE INGREDIENTS: POTASSIUM CHLORIDE 1.125 g/1.185 g
INACTIVE INGREDIENTS: SILICON DIOXIDE; ANHYDROUS CITRIC ACID; FD&C YELLOW NO. 6; SUCRALOSE

HIGHLIGHTS OF PRESCRIBING INFORMATION

These highlights do not include all the information needed to use POKONZA® safely and effectively. See full prescribing information for POKONZA®.
POKONZA® (Potassium Chloride for Oral Solution, USP)
Initial U.S. Approval: 1948

1 INDICATIONS AND USAGE

POKONZA® (Potassium Chloride for Oral Solution, USP) is a potassium salt indicated for the treatment and prophylaxis of hypokalemia with or without metabolic alkalosis, in patients for whom dietary management with potassiumrich foods or diuretic dose reduction is insufficient. (1)

2 DOSAGE AND ADMINISTRATION

Dilute prior to administration. (2.1, 5.1)

Monitor serum potassium and adjust dosage accordingly (2.2, 2.3)

If serum potassium concentration is <2.5 mEq/L, use intravenous potassium instead of oral supplementation (2.1)

Treatment of hypokalemia:

- Adults: Initial doses range from 40-100 mEq/day in 2-5 divided doses: limit doses to 40 mEq per dose. Total daily dose should not exceed 200 mEq (2.2)
- Pediatric patients aged birth to 16 years old: 2-4 mEq/kg/day in divided doses; not to exceed 1 mEq/kg as a single dose or 40 mEq whichever is lower; if deficits are severe or ongoing losses are great, consider intravenous therapy. Total daily dose should not exceed 100 mEq (2.3)

Maintenance or Prophylaxis of hypokalemia:

- Adults: Typical dose is 20 mEq per day (2.2)
- Pediatric patients aged birth to 16 years old: typical dose is 1 mEq/kg/day.
  Do not exceed 3 mEq/kg/day (2.3)

3 DOSAGE FORMS AND STRENGTHS

POKONZA® (Potassium Chloride for Oral Solution, USP), is a light pink to orange powder available in two strengths as follows:

- 10 mEq: Each pouch contains 0.75 g of Potassium Chloride providing potassium 10 mEq and chloride 10 mEq. (3)
- 15 mEq: Each pouch contains 1.185 g of Potassium Chloride providing potassium 15 mEq and chloride 15 mEq. (3)

4 CONTRAINDICATIONS

- Concomitant use with potassium sparing diuretics. (4)

5 WARNINGS AND PRECAUTIONS

- Gastrointestinal Irritation: Dilute before use, take with meals (5.1)

6 ADVERSE REACTIONS

Most common adverse reactions are nausea, vomiting, flatulence, abdominal pain/discomfort, and diarrhea. (6)

To report SUSPECTED ADVERSE REACTIONS, contact Carwin Pharmaceutical Associates at 1-844-700-5011 or FDA at 1-800-FDA-1088 or www.fda.gov/ medwatch.

7 DRUG INTERACTIONS

- Potassium sparing diuretics: Avoid concomitant use (7.1)
- Renin-angiotensin-aldosterone inhibitors: Monitor for hyperkalemia (7.2)
- Nonsteroidal Anti-Inflammatory drugs: Monitor for hyperkalemia (7.3)

8 USE IN SPECIFIC POPULATIONS

Cirrhosis: Initiate therapy at the low end of the dosing range (8.5)

Renal Impairment: Initiate therapy at the low end of the dosing range (8.6)

FULL PRESCRIBING INFORMATION

1 INDICATIONS AND USAGE

POKONZA® (Potasium Chloride for Oral Solution, USP) is indicated for the treatment and prophylaxis of hypokalemia with or without metabolic alkalosis, in patients for whom dietary management with potassium-rich foods or diuretic dose reduction is insufficient.

2 DOSAGE AND ADMINISTRATION

2.1 Administration and Monitoring

Monitoring

Monitor serum potassium and adjust dosages accordingly. For treatment of hypokalemia, monitor potassium levels daily or more often depending on the severity of hypokalemia until they return to normal. Monitor potassium levels monthly to biannually for maintenance or prophylaxis.

The treatment of potassium depletion, particularly in the presence of cardiac disease, renal disease, or acidosis requires careful attention to acid-base balance, volume status, electrolytes, including magnesium, sodium, chloride, phosphate, and calcium, electrocardiograms and the clinical status of the patient. Correct volume status, acid-base balance and electrolyte deficits as appropriate.

Administration

Dilute the contents of 1 pouch of POKONZA® in at least 4 ounces of cold water [see Warnings and Precautions (5.1)].

Take with meals or immediately after eating.

If serum potassium concentration is <2.5 mEq/L, use intravenous potassium instead of oral supplementation.

2.2 Adult Dosing

Treatment of hypokalemia:

Daily dose range from 40 to 100 mEq. Give in 2 to 5 divided doses: limit doses to 40 mEq per dose. The total daily dose should not exceed 200 mEq in a 24 hour period.

Maintenance or Prophylaxis

Typical dose is 20 mEq per day. Individualize dose based upon serum potassium levels.

Studies support the use of potassium replacement in digitalis toxicity. When alkalosis is present, normokalemia and hyperkalemia may obscure a total potassium deficit. The advisability of use of potassium replacement in the setting of hyperkalemia is uncertain.

2.3 Pediatric Dosing

Treatment of hypokalemia:

Pediatric patients aged birth to 16 years old: The initial dose is 2 to 4 mEq/kg/day in divided doses; do not exceed as a single dose 1 mEq/kg or 40 mEq, whichever is lower; maximum daily doses should not exceed 100 mEq. If deficits are severe or ongoing losses are great, consider intravenous therapy.

Maintenance or Prophylaxis

Pediatric patients aged birth to 16 years old: Typical dose is 1 mEq/kg/day. Do not exceed 3 mEq/kg/day.

3 DOSAGE FORMS AND STRENGTHS

POKONZA® (Potassium Chloride for Oral Solution, USP), is a light pink to orange powder available in two strengths as follows:

Each 10 mEq pouch contains 0.75 g of potassium chloride supplying 10 mEq of potassium and 10 mEq of chloride.

Each 15 mEq pouch contains 1.185 g of potassium chloride supplying 15 mEq of potassium and 15 mEq of chloride.

4 CONTRAINDICATIONS

POKONZA® is contraindicated in patients on potassium sparing diuretics.

5 WARNINGS AND PRECAUTIONS

5.1 Gastrointestinal Irritation

May cause gastrointestinal irritation. Increased dilution of the solution and taking with meals may reduce gastrointestinal irritation [see Dosage and Administration (2.1)].

6 ADVERSE REACTIONS

The most common adverse reactions to oral potassium salts are nausea, vomiting, flatulence, abdominal pain/discomfort, and diarrhea.

7 DRUG INTERACTIONS

7.1 Potassium-Sparing Diuretics

Use with potassium-sparing diuretics can produce severe hyperkalemia. Avoid concomitant use.

7.2 Renin-Angiotensin-Aldosterone System Inhibitors

Drugs that inhibit the renin-angiotensin-aldosterone system (RAAS) including angiotensin converting enzyme (ACE) inhibitors, angiotensin receptor blockers (ARBs), spironolactone, eplerenone, or aliskiren produce potassium retention by inhibiting aldosterone production. Closely monitor potassium in patients receiving concomitant RAAS therapy.

7.3 Nonsteroidal Anti-Inflammatory Drugs (NSAIDs)

NSAIDs may produce potassium retention by reducing renal synthesis of prostaglandin E and impairing the renin-angiotensin system. Closely monitor potassium in patients on concomitant NSAIDs.

8 USE IN SPECIFIC POPULATIONS

8.1 Pregnancy

There are no human data related to use of POKONZA® during pregnancy, and animal studies have not been conducted. Potassium supplementation that does not lead to hyperkalemia is not expected to cause fetal harm.

The background risk for major birth defects and miscarriage in the indicated population is unknown. All pregnancies have a background risk of birth defect, loss, or other adverse outcomes. In the U.S. general population, the estimated background risk of major birth defects and miscarriage in clinically recognized pregnancies is 2-4% and 15-20%, respectively.

8.2 Lactation

Risk Summary

The normal potassium ion content of human milk is about 13 mEq per liter. Since potassium from oral supplements such as POKONZA® becomes part of the body potassium pool, as long as body potassium is not excessive, the contribution of potassium chloride supplementation should have little or no effect on the level in human milk.

8.4 Pediatric Use

Clinical trial data from published literature have demonstrated the safety and effectiveness of potassium chloride in children with diarrhea and malnutrition from birth to 16 years.

8.5 Geriatric Use

Clinical studies of POKONZA® did not include sufficient numbers of subjects aged 65 and over to determine whether they respond differently from younger subjects. Other reported clinical experience has not identified differences in responses between the elderly and younger patients. In general, dose selection for an elderly patient should be cautious, usually starting at the low end of the dosing range, reflecting the greater frequency of decreased hepatic, renal, or cardiac function, and of concomitant disease or other drug therapy.

This drug is known to be substantially excreted by the kidney, and the risk of toxic reactions to this drug may be greater in patients with impaired renal function. Because elderly patients are more likely to have decreased renal function, care should be taken in dose selection, and it may be useful to monitor renal function.

8.6 Cirrhotics

Patients with cirrhosis should usually be started at the low end of the dosing range, and the serum potassium level should be monitored frequently. [see Clinical Pharmacology (12.3)].

8.7 Renal Impairment

Patients with renal impairment have reduced urinary excretion of potassium and are at substantially increased risk of hyperkalemia. Patients with impaired renal function, particularly if the patient is on ACE inhibitors, ARBs, or nonsteroidal antiinflammatory drugs should usually be started at the low end of the dosing range because of the potential for development of hyperkalemia. The serum potassium level should be monitored frequently. Renal function should be assessed periodically.

10 OVERDOSAGE

10.1 Symptoms

The administration of oral potassium salts to persons with normal excretory mechanisms for potassium rarely causes serious hyperkalemia. However, if excretory mechanisms are impaired or if potassium is administered too rapidly potentially fatal hyperkalemia can result.

Hyperkalemia is usually asymptomatic and may be manifested only by an increased serum potassium concentration (6.5–8.0 mEq/L) and characteristic electrocardiographic changes (peaking of T-waves, loss of P-waves, depression of S-T segment, and prolongation of the QT-interval). Late manifestations include muscle paralysis and cardiovascular collapse from cardiac arrest (9-12 mEq/L).

10.2 Treatment

Treatment measures for hyperkalemia include the following:

1. Monitor closely for arrhythmias and electrolyte changes.
2. Eliminate foods and medications containing potassium and of any agents with potassium-sparing properties such as potassium-sparing diuretics, ARBs, ACE inhibitors, NSAIDs, certain nutritional supplements and many others.
3. Administer intravenous calcium gluconate if the patient is at no risk or low risk of developing digitalis toxicity.
4. Administer intravenously 300 to 500 mL/hr of 10% dextrose solution containing 10 to 20 units of crystalline insulin per 1000 mL.
5. Correct acidosis, if present, with intravenous sodium bicarbonate.
6. Use exchange resins, hemodialysis, or peritoneal dialysis.
  In patients who have been stabilized on digitalis, too rapid a lowering of the serum potassium concentration can produce digitalis toxicity.

11 DESCRIPTION

Potassium Chloride is a white crystalline or colorless solid. It is soluble in water and slightly soluble in alcohol. Chemically, Potassium Chloride is K-Cl with a molecular mass of 74.55.

Each pouch of POKONZA® (Potassium Chloride for Oral Solution, USP) is a light pink to orange powder containing:

- 10 mEq: contains 0.75 g of potassium chloride, USP, which is equivalent to potassium 10 mEq and chloride 10 mEq and the following inactive ingredients: citric acid anhydrous, colloidal silicon dioxide, FD&C Yellow #6, natural and artificial orange flavor, and sucralose.
- 15 mEq: contains 1.185 g of potassium chloride, USP, which is equivalent to potassium 15 mEq and chloride 15 mEq and the following inactive ingredients: citric acid anhydrous, colloidal silicon dioxide, FD&C Yellow #6, natural and artificial orange flavor, and sucralose.

12 CLINICAL PHARMACOLOGY

12.1 Mechanism of Action

The potassium ion (K^+) is the principal intracellular cation of most body tissues. Potassium ions participate in a number of essential physiological processes including the maintenance of intracellular tonicity; the transmission of nerve impulses; the contraction of cardiac, skeletal, and smooth muscle; and the maintenance of normal renal function.

The intracellular concentration of potassium is approximately 150 to 160 mEq per liter. The normal adult plasma concentration is 3.5 to 5 mEq per liter. An active ion transport system maintains this gradient across the plasma membrane.

Potassium is a normal dietary constituent, and under steady-state conditions the amount of potassium absorbed from the gastrointestinal tract is equal to the amount excreted in the urine. The usual dietary intake of potassium is 50 to 100 mEq per day.

12.3 Pharmacokinetics

Based on published literature, the rate of absorption and urinary excretion of potassium from KCl oral solution were higher during the first few hours after dosing relative to modified release KCl products. The bioavailability of potassium, as measured by the cumulative urinary excretion of K^+ over a 24 hour post dose period, is similar for KCl solution and modified release products.

Specific Populations

Cirrhotics

Based on published literature, the baseline corrected serum concentrations of potassium measured over 3 h after administration in cirrhotic subjects who received an oral potassium load rose to approximately twice that of normal subjects who received the same load.

16 HOW SUPPLIED/STORAGE AND HANDLING

POKONZA® (Potassium Chloride for Oral Solution, USP), is a light pink to orange powder available in two strengths as follows:

10 mEq

NDC# 15370-305-01 pouch. Each pouch contains 0.75 g of potassium chloride providing potassium 10 mEq and chloride 10 mEq

NDC# 15370-305-60 | 1 carton of 60 pouches
NDC# 15370-305-30 | 1 carton of 30 pouches

15 mEq

NDC# 15370-306-01 pouch: Each pouch contains 1.185 g of potassium chloride providing potassium 15 mEq and chloride 15 mEq

NDC# 15370-306-60 | 1 carton of 60 pouches
NDC# 15370-306-30 | 1 carton of 30 pouches

Storage

Store at Controlled Room Temperature, 25°C (77°F); excursions are permitted to 15°C to 30°C (59°F to 86°F).

Dispense in a tight, light-resistant container as defined in the USP.

Protect from Light.

Rx only

Distributed by:
Carwin Pharmaceutical Associates, LLC.
Hazlet, NJ 07730

Revised: November 2025

PRINCIPAL DISPLAY PANEL - 1.185 g Pouch Carton

NDC 15370-306-30

POKONZA®
(Potassium Chloride
for Oral Solution, USP)

15 mEq

Orange Flavored

Each pouch contains: Potassium Chloride 1.185 g

30 Single-Dose Pouches
Rx Only